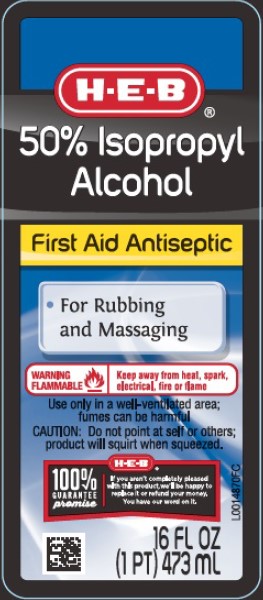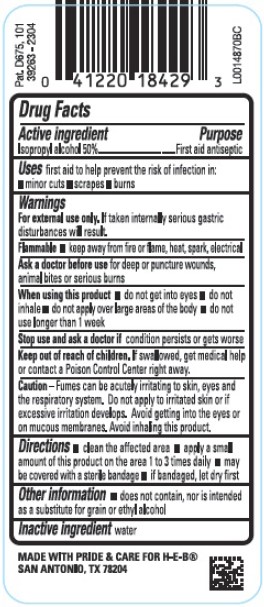 DRUG LABEL: 50% Isopropyl Alcohol
NDC: 59640-864 | Form: SOLUTION
Manufacturer: H E B
Category: otc | Type: HUMAN OTC DRUG LABEL
Date: 20260224

ACTIVE INGREDIENTS: ISOPROPYL ALCOHOL 50 mL/100 mL
INACTIVE INGREDIENTS: WATER

HEB 864.003/864AA-AC
50% Isopropyl Alcohol

Active ingredient

Isopropyl alcohol 50%

Purpose

First Aid Antiseptic

Uses

first aid to help prevent the risk of infection in:

- minor cuts
- scrapes
- burns

Warnings

For external use only. If taken internally serious gastric disturbances will result.

Flammable keep away from fire or flame, heat, spark, electrical.

Ask a doctor before use

for deep or pucture wounds, animal bites or serious burns

When using this product

- do not get into eyes
- do not inhale
- do not apply over large areas of teh body
- do not use longer than 1 week

Stop use and ask a doctor if

condition persists or gets worse

Keep out of reach of children.

If swallowed, get medical help or contact a Poison Control Center right away.

Caution

Fumes can be acutely irritating to skin, eyes and the respiratory system. Do not apply to irritated skin or if excessive irritation develops. Avoid getting into the eyes or on mucous membranes. Avoid inhaling this product.

Directions

- clean the affected area
- apply a small amount of this product on the area 1 to 3 times a day
- may be covered with a sterile bandage
- if bandaged, let dry first

Other information

- does not contain, nor is intended as a substitute for grain or ethyl alcohol

Inactive ingredient

water

ADVERSE REACTION

MADE WITH PRIDE & CARE FOR H-E-B®

SAN ANTONIO, TX 78204

Pat. D675,101

principal display panel

H-E-B®

50% Isopropyl Alcohol

First Aid Antiseptic

- for rubbing and massaging

WARNING FLAMMABLE - Keep away from heat, spark, electrical, fire or flame

Use ony in a well-ventilated area; fumes can be harmful

CAUTION: Do not point at self or others; product will squirt when squeezed.

H-E-B® 100% Guarantee promise

If you arn't completely pleased with this product, we'll be happy to replace it or refund your money You have our word on it.

16 FL OZ (1 PT) 473 mL